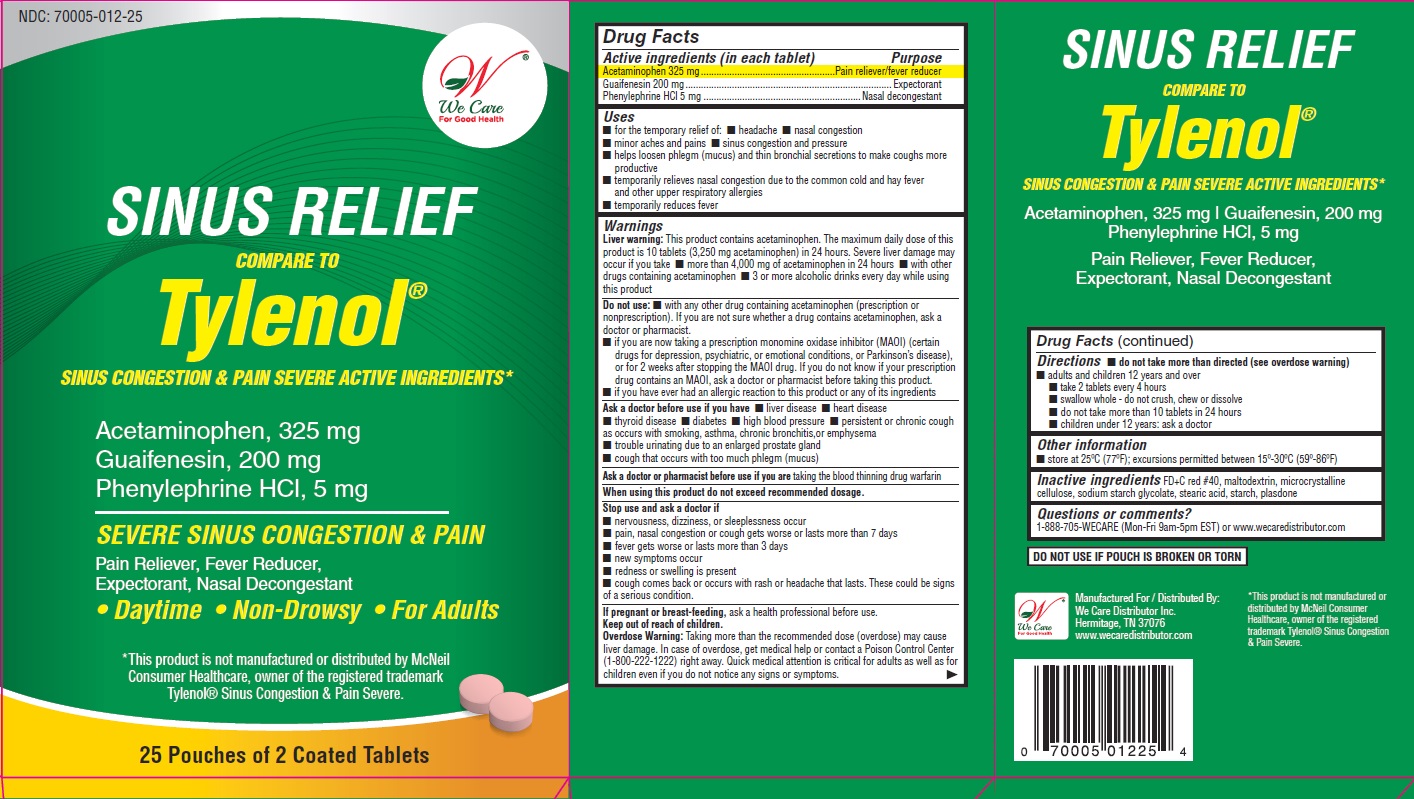 DRUG LABEL: SINUS CONGESTION AND PAIN RELIEF
NDC: 70005-012 | Form: Tablet, coated
Manufacturer: We Care Distributor Inc.
Category: otc | Type: HUMAN OTC DRUG LABEL
Date: 20191001

ACTIVE INGREDIENTS: ACETAMINOPHEN 325 mg/1 1; GUAIFENESIN 200 mg/1 1; PHENYLEPHRINE HYDROCHLORIDE 5 mg/1 1
INACTIVE INGREDIENTS: FD&C RED NO. 40; MALTODEXTRIN; CELLULOSE, MICROCRYSTALLINE; SODIUM STARCH GLYCOLATE TYPE A POTATO; STEARIC ACID; STARCH, CORN; POVIDONE

SINUS CONGESTION AND PAIN RELIEF - Acetaminophen, Guaifenesinand Phenylephrine HCl

Drug Facts

ACTIVE INGREDIENT

Active Ingredient (in each tablet) | Purpose
Acetaminophen 325 mg | Pain reliever/fever reducer
Guaifenesin 200 mg | Expectorant
Phenylephrine HCl 5 mg | Nasal decongestant

Uses

- for the temporary relief of:
- headache
- nasal congestion
- minor aches and pains
- sinus congestion and pressure
- helps loosen phlegm (mucus) and thin bronchial secretions to make coughs more productive
- temporarily relieves nasal congestion due to the common cold and hay fever and other upper respiratory allergies
- temporarily reduces fever

Warnings

Liver warning:

This product contains acetaminophen. The maximum daily dose of this product is 10 tablets (3,250 mg acetaminophen) in 24 hours. Severe liver damage may occur if you take

- more than 4,000 mg of acetaminophen in 24 hours
- with other drugs containing acetaminophen
- 3 or more alcoholic drinks every day while using this product

Do not use

- with any other drug containing acetaminophen (prescription or nonprescription). If you are not sure whether a drug contains acetaminophen, ask a doctor or pharmacist
- if you are now taking a prescription monomine oxidase inhibitor (MAOI) (certain drugs for depression, psychiatric, or emotional conditions, or Parkinson’s disease), or for 2 weeks after stopping the MAOI drug. If you do not know if your prescription drug contains an MAOI, ask a doctor or pharmacist before taking this product
- if you have ever had an allergic reaction to this product or any of its ingredients

Ask a doctor before use if you have

- liver disease
- heart disease
- thyroid disease
- diabetes
- high blood pressure
- persistent or chronic cough as occurs with smoking, asthma, chronic bronchitis,or emphysema
- trouble urinating due to an enlarged prostate gland
- cough that occurs with too much phlegm (mucus)

Ask a doctor or pharmacist before use if you are

- taking the blood thinning drug warfarin

When using this product

do not exceed recommended dosage

Stop use and ask a doctor if

- nervousness, dizziness, or sleeplessness occur
- pain, nasal congestion or cough gets worse or lasts more than 7 days
- fever gets worse or lasts more than 3 days
- new symptoms occur
- redness or swelling is present
- cough comes back or occurs with rash or headache that lasts

These could be signs of a serious condition

PREGNANCY OR BREAST FEEDING

If pregnant or breast-feeding, ask a health professional before use.

Keep out of reach of children.

Overdose Warning: Taking more than the recommended dose (overdose) may cause liver damage. In case of overdose, get medical help or contact a Poison Control Center (1-800-222-1222) right away. Quick medical attention is critical for adults as well as for children even if you do not notice any signs or symptoms.

Directions

- do not take more than directed (see overdose warning)
- adults and children 12 years and over:
- take 2 tablets every 4 hours
- swallow whole - do not crush, chew or dissolve
- do not take more than 10 tablets in 24 hours
- children under 12 years: ask a doctor

Other information

- store at 25ºC (77ºF); excursions permitted between 15º-30ºC (59º-86ºF)
- read all product information before using. Keep this box for important information

Inactive ingredients

FD&C red #40, maltodextrin, microcrystalline cellulose, povidone, sodium starch glycolate, starch, stearic acid

Questions or comments?

1-888-705-WECARE (Mon-Fri 9am-5pm EST) or www.wecaredistributor.com

PRINCIPAL DISPLAY PANEL

See New Warnings Information & Directions

Compare to the Active Ingredients in

Tylenol® Sinus Congestion & Pain Severe

Acetaminophen, Guaifenesin and Phenylephrine HCl 325 mg, 200 mg and 5 mg

TO OPEN
PUSH IN TAB AND PULL OUT

25 Pouches of 2 Tablets Each